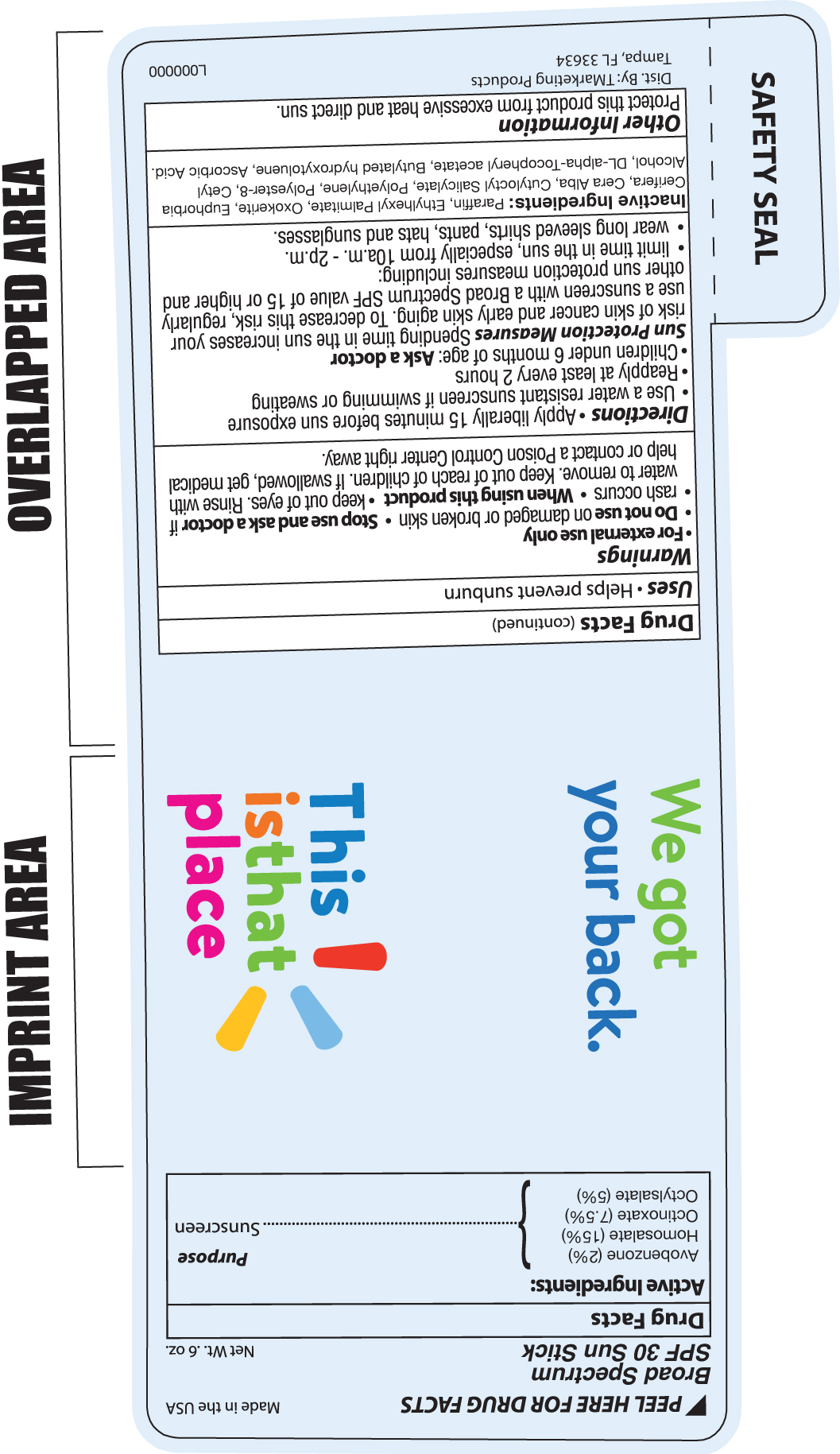 DRUG LABEL: FT SPF30 Sun Stick
NDC: 58418-275 | Form: STICK
Manufacturer: Tropical Enterprises International, Inc
Category: otc | Type: HUMAN OTC DRUG LABEL
Date: 20180828

ACTIVE INGREDIENTS: OCTINOXATE 7.5 mg/1 mL; HOMOSALATE 15 mg/1 mL; OCTISALATE 5 mg/1 mL; AVOBENZONE 2 mg/1 mL
INACTIVE INGREDIENTS: WHITE WAX; .ALPHA.-TOCOPHEROL ACETATE; PARAFFIN; ETHYLHEXYL PALMITATE; BUTYLOCTYL SALICYLATE; POLYESTER-8 (1400 MW, CYANODIPHENYLPROPENOYL CAPPED); BUTYLATED HYDROXYTOLUENE; ASCORBIC ACID; CANDELILLA WAX; CETYL ALCOHOL; POLYETHYLENE GLYCOL, UNSPECIFIED; CERESIN

FT Broad Spectrum Spf30 Sunstick 275

ACTIVE INGREDIENT

Avobenzone 2%

Octyl Salate 5%

Homosalate 15%

Octinoxate 7.5%

PURPOSE

Uses * Helps prevent sunburn

Warnings

- For external use only
- Do not use on damaged or broken skin
- Stop use and ask a doctor if rash occurs
- When using this product keep out of eyes. Rinse with water to remove
- Keep out of reach of children. If produict is swallowed get medical help or contact a Poison Control Center right away.

INSTRUCTIONS FOR USE

Directions: Apply liberally 15 minutes before sun exposure

- Use a water resistant sunscreen if swimming or sweating
- Reapply at least every 2 hours
- Children under 6 months of age: Ask a doctor

Sun Protection Measures: Spending time in the sun increases your risk of skin cancer and early skin aging.

To decrease this risk, reguarly use a sunscreen with a Broad Spectrum SPF value of 15 or higher and other sun protection measures including:

- limit time in the sun, especially from 10a.m. - 2p.m.
- wear long sleeved shirts, pants, hats and sunglasses

INACTIVE INGREDIENT

Inactive Ingredients: Parrafin, Ethylhexyl Palmitate, Oxokerite, Ephorbia Cerifera, Cera Alba, Cutyloctyl Sallicylate, Polyethylene, Polyester-8, Cetyl Alcohol, DL-alpha-Tocopheryl acetate, Butylated hydroxytoluene, Ascorbic Acid

Other Information

Protect this product from excessive heat and direct sun.